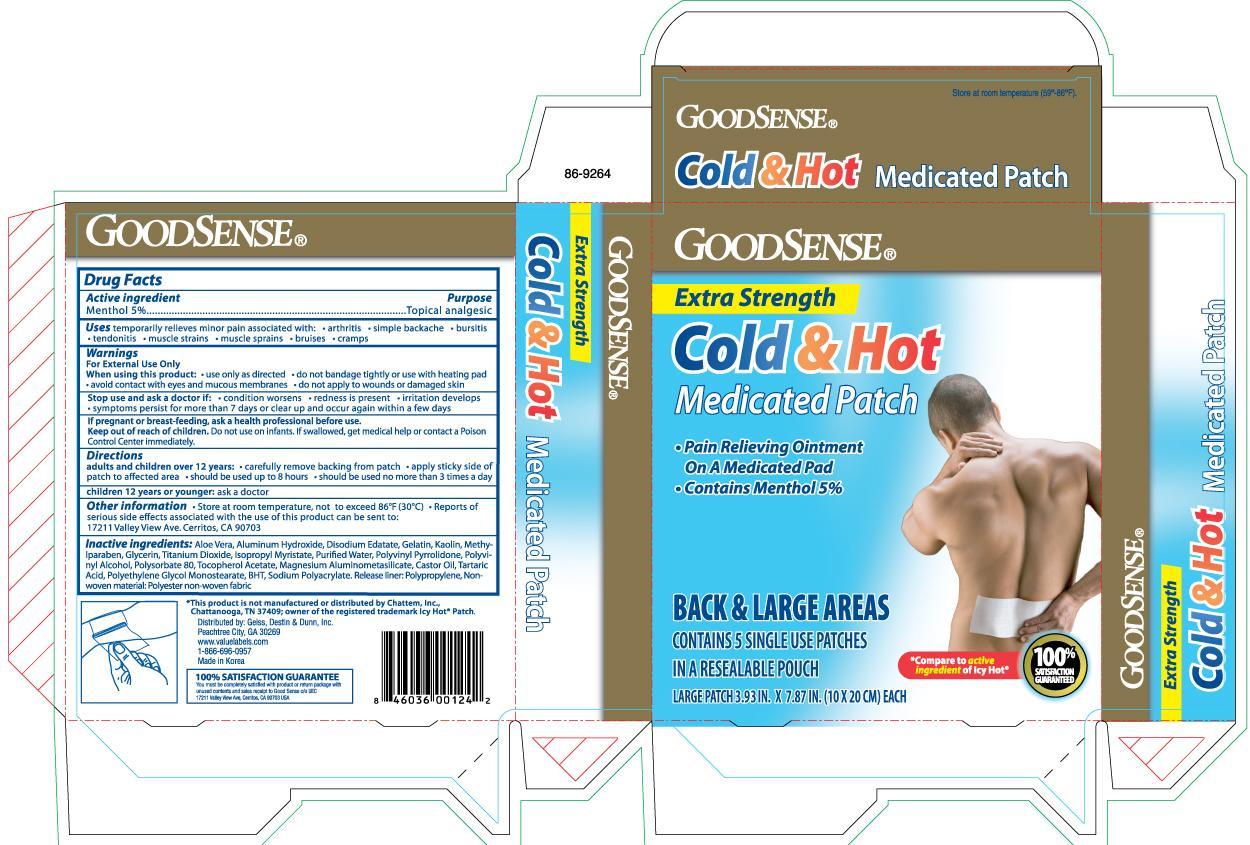 DRUG LABEL: Goodsense Extra Strength Cold and Hot Medicated
NDC: 75981-124 | Form: PATCH
Manufacturer: Geiss, Destin and Dunn, Inc.
Category: otc | Type: HUMAN OTC DRUG LABEL
Date: 20130630

ACTIVE INGREDIENTS: MENTHOL 750 mg/1 1
INACTIVE INGREDIENTS: ALOE VERA LEAF; ALUMINUM HYDROXIDE; GELATIN; KAOLIN; METHYLPARABEN; GLYCERIN; TITANIUM DIOXIDE; ISOPROPYL MYRISTATE; WATER; POLYVINYL ALCOHOL; POLYSORBATE 80; ALPHA-TOCOPHEROL ACETATE; CASTOR OIL; TARTARIC ACID; BUTYLATED HYDROXYTOLUENE

Drug Facts

Active ingredient Purpose

Menthol 5%..........................................................Topical analgesic

PURPOSE

Uses temporarily relieves minor pain associated with:

- arthritis
- simple backache
- bursitis
- tendonitis
- muscle strains
- muscle sprains
- bruises
- cramps

Warnings For External Use Only

When using this product:

- use only as directed
- do not bandage tightly or use with heating pad
- avoid contact with eyes and mucous membranes
- do not apply to wounds or damaged skin

Stop use and ask a doctor if:

- condition worsens
- redness is present
- irritation develops
- symptoms persist for more than 7 days or clear up and occur again within a few days

PREGNANCY OR BREAST FEEDING

If pregnant or breast-feeding, ask a health professional before use.

Keep out of reach of children. Do not use on infants. If swallowed, get medical help or contact a Poison Control Center immediately.

Directions

- adults and children over 12 years:
- carefully remove backing from patch
- apply sticky side of patch to affected area
- should be used up to 8 hours
- should be used no more than 3 times a day
- children 12 years or younger: ask a doctor

Other information

- Store at room temperature, not to exceed 86°F (30°C)
- Reports of serious side effects associated with the use of this product can be sent to:
- 17211 Valley View Ave. Cerritos, CA 90703

INACTIVE INGREDIENT

Inactive ingredients: Aloe Vera, Aluminum Hydroxide, Disodium Edate, Gelatin, Kaolin, Methylparaben, Glycerin, Titanium dioxide, Isopropyl Myristate, Purified Water, Polyvinyl Pyrrolidone, Polyvinyl Alcohol, Polysorbate 80, Tocopherol Acetate, Magnesium Aluminometasilicate, Castor Oil, Tartaric Acid, Polyethylene Glycol Monostearate, BHT, Sodium POlyacrylate. Release liner: Polypropylene, Non-woven material: Polyester non-woven fabric

DOSAGE AND ADMINISTRATION

Distributed by: Geiss, Destin and Dunn, Inc.

Peachtree City, GA 30269

Made in Korea